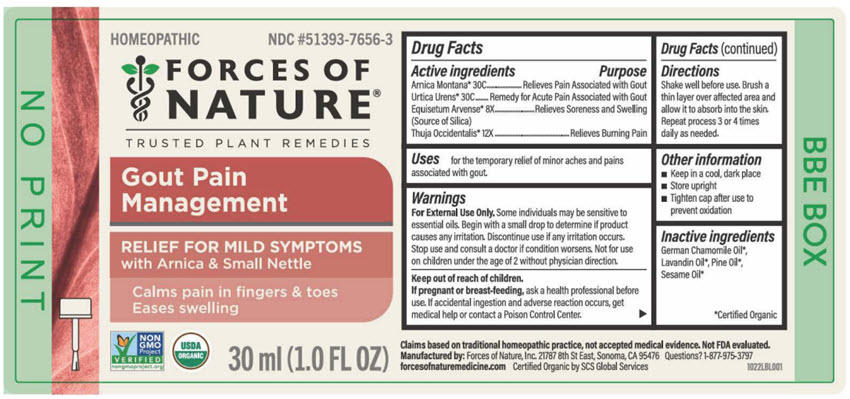 DRUG LABEL: Gout 
NDC: 51393-7656 | Form: SOLUTION/ DROPS
Manufacturer: Forces of Nature
Category: homeopathic | Type: HUMAN OTC DRUG LABEL
Date: 20251125

ACTIVE INGREDIENTS: ARNICA MONTANA WHOLE 30 [hp_C]/1000 mL; URTICA URENS WHOLE 30 [hp_C]/1000 mL; Silicon Dioxide 8 [hp_X]/1000 mL; Thuja Occidentalis Leaf 12 [hp_X]/1000 mL
INACTIVE INGREDIENTS: Sesame Oil; Pine Needle Oil (Pinus Sylvestris); Lavandin Oil; Chamomile Flower Oil

Gout
Pain Management

PAIN MANAGEMENT DRUG FACTS

ACTIVE INGREDIENT

PURPOSE

Active Ingredients

Arnica Montana [USDA Certified Organic] 30C - Relieves Pain Associated with Gout

Urtica Urens 30C - Remedy for Acute Pain Associated with Gout

Silicea 8X - Relieves Soreness and Swelling

Thuja Occidentalis 12X - Relieves Burning Pain

Also Contains

Sesame Oil, Pine Oil, Lavandin Oil, German Chamomile Oil

Indications

Topical Analgesic: For the temporary relief of minor aches and pains associated with gout.

Directions

Shake well before use. Apply to affected area by gently rubbing into the skin up to 3 or 4 times daily. For children under 2 years of age, consult a doctor before use.

Warnings

Some individuals may be sensitive to essential oils. Begin with a small drop to determine if the product causes any increased redness or irritation and discontinue use if it irritates your skin. For external use only. If accidental ingestion of more than several drops, and adverse reaction occurs, get medical help or contact a Poison Control Center. Do not apply to the eyes. If you are pregnant or breast-feeding, ask a health professional before use. Not for use on children under the age of 2 without physician direction.

KEEP OUT OF REACH OF CHILDREN

Keep all medicines out of the reach of children. Stop use and consult a doctor if condition worsens, or consult a doctor if symptoms show no improvement after 7 days.

Tips For Use

Gout Pain Management is exclusively designed to help ease painful joints and toes from gout. It contains 100% natural and organic topical analgesics.

Product is to be applied 3-5 times per day directly to the affected area while symptoms exist. Simply allow 2-3 drops of product to absorb into problem area by gently rubbing it into the skin.

Gout is a serious medical condition and it is important to consult your doctor should you think you suffer from the ailment.

Manufactured & Distributed by
FORCES OF NATURE®
21787 8th St East #3A Sonoma, CA 95476 USA

PRINCIPAL DISPLAY PANEL - 30 ml Bottle Label

HOMEOPATHIC
NDC #51393-7656-3

FORCES OF
NATURE®

TRUSTED PLANT REMEDIES

Gout Pain
Management

RELIEF FOR MILD SYMPTOMS
with Arnica & Small Nettle

Calms pain in fingers & toes
Eases swelling

NON
GMO
Project
VERIFIED
nongmoproject.org

USDA
ORGANIC

30 ml (1.0 FL OZ)